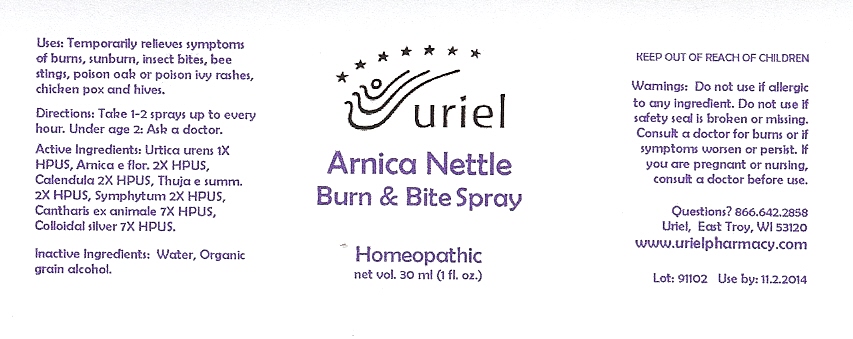 DRUG LABEL: Arnica Nettle Burn and Bite
NDC: 48951-1149 | Form: SPRAY
Manufacturer: Uriel Pharmacy Inc
Category: homeopathic | Type: HUMAN OTC DRUG LABEL
Date: 20100317

ACTIVE INGREDIENTS: URTICA URENS 1 [hp_X]/1 1; CALENDULA OFFICINALIS FLOWERING TOP 2 [hp_X]/1 1; ARNICA MONTANA FLOWER 2 [hp_X]/1 1; COMFREY 2 [hp_X]/1 1; THUJA OCCIDENTALIS TWIG 2 [hp_X]/1 1; LYTTA VESICATORIA 7 [hp_X]/1 1; SILVER 7 [hp_X]/1 1
INACTIVE INGREDIENTS: ALCOHOL; WATER

Arnica Nettle Burn & Bite Spray- 1 oz.

Purpose

Uses: Temporarily relieves symptoms of burns, sunburn, insect bites, bee stings, poison oak or poison ivy rashes, chicken pox and hives.

Dosage & Administration

Directions: Take 1-2 sprays up to every hour. Under age 2: Ask a doctor.

OTC-Active Ingredient

Active Ingredients: Urtica urens 1X HPUS, Arnica e flor. 2X HPUS, Calendula 2X HPUS, Thuja e summ. 2X HPUS, Symphytum 2X HPUS, Cantharis ex animale 7X HPUS, Colloidal silver 7X HPUS.

Inactive Ingredient

Inactive Ingredients: Water, Organic grain alcohol.

Keep out of reach of children

Do not use section

Warnings: Do not use if allergic to any ingredient. Do not use if safety seal is broken or missing.

Ask doctor section

Consult a doctor for burns or if symptoms worsen or persist.

Pregnancy or breast feeding section

If you are pregnant or nursing, consult a doctor before use.

Questions section

Questions? Uriel Pharmacy

866 642-2858 East Troy, WI 53120

www.urielpharmacy.com

Principal Display Panel

Arnica Nettle

Burn and Bite Spray

Homeopathic

net vol. 30 ml (1 fl. oz.)